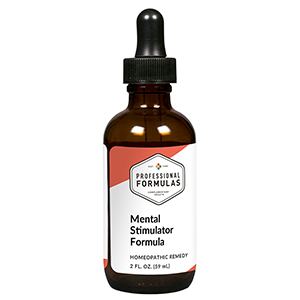 DRUG LABEL: Mental Stimulator Formula
NDC: 63083-2071 | Form: LIQUID
Manufacturer: Professional Complementary Health Formulas
Category: homeopathic | Type: HUMAN OTC DRUG LABEL
Date: 20190815

ACTIVE INGREDIENTS: HIPPOCAMPUS KUDA 3 [hp_X]/59 mL; ASIAN GINSENG 3 [hp_X]/59 mL; CORNUS OFFICINALIS FRUIT 3 [hp_X]/59 mL; CYNOMORIUM SONGARICUM STEM 3 [hp_X]/59 mL; ANGELICA ACUTILOBA ROOT 3 [hp_X]/59 mL; EPIMEDIUM WUSHANENSE WHOLE 3 [hp_X]/59 mL
INACTIVE INGREDIENTS: ALCOHOL; WATER

C71

ACTIVE INGREDIENTS

all the following at 3X, 6X, 12X, 30X:
Hai-Ma
Jen-Shen
Shan-Chu-Yu
So-Yang
Tang-Kuei
Yin-Yang-Huo

QUESTIONS

Professional Formulas

PO Box 2034 Lake Oswego, OR 97035

INDICATIONS

For the temporary relief of weak memory, anxiousness, irritability, or mood swings.*

PURPOSE

*Claims based on traditional homeopathic practice, not accepted medical evidence. Not FDA evaluated.

WARNINGS

In case of overdose, get medical help or contact a poison control center right away.

Keep out of the reach of children.

PREGNANCY OR BREAST FEEDING

If pregnant or breastfeeding, ask a healthcare professional before use.

DIRECTIONS

Place drops under tongue 30 minutes before/after meals. Adults and children 12 years and over: Take 10 drops up to 3 times per day. Consult a physician for use in children under 12 years of age.

OTHER INFORMATION

Tamper resistant. If seal is broken, do not use. After opening, close container tightly and store at room temperature away from heat.

INACTIVE INGREDIENTS

20% ethanol, purified water.

LABEL

Est 1985

Professional Formulas

Complementary Health

Mental Stimulator Formula

Homeopathic Remedy

2 FL. OZ. (59 mL)